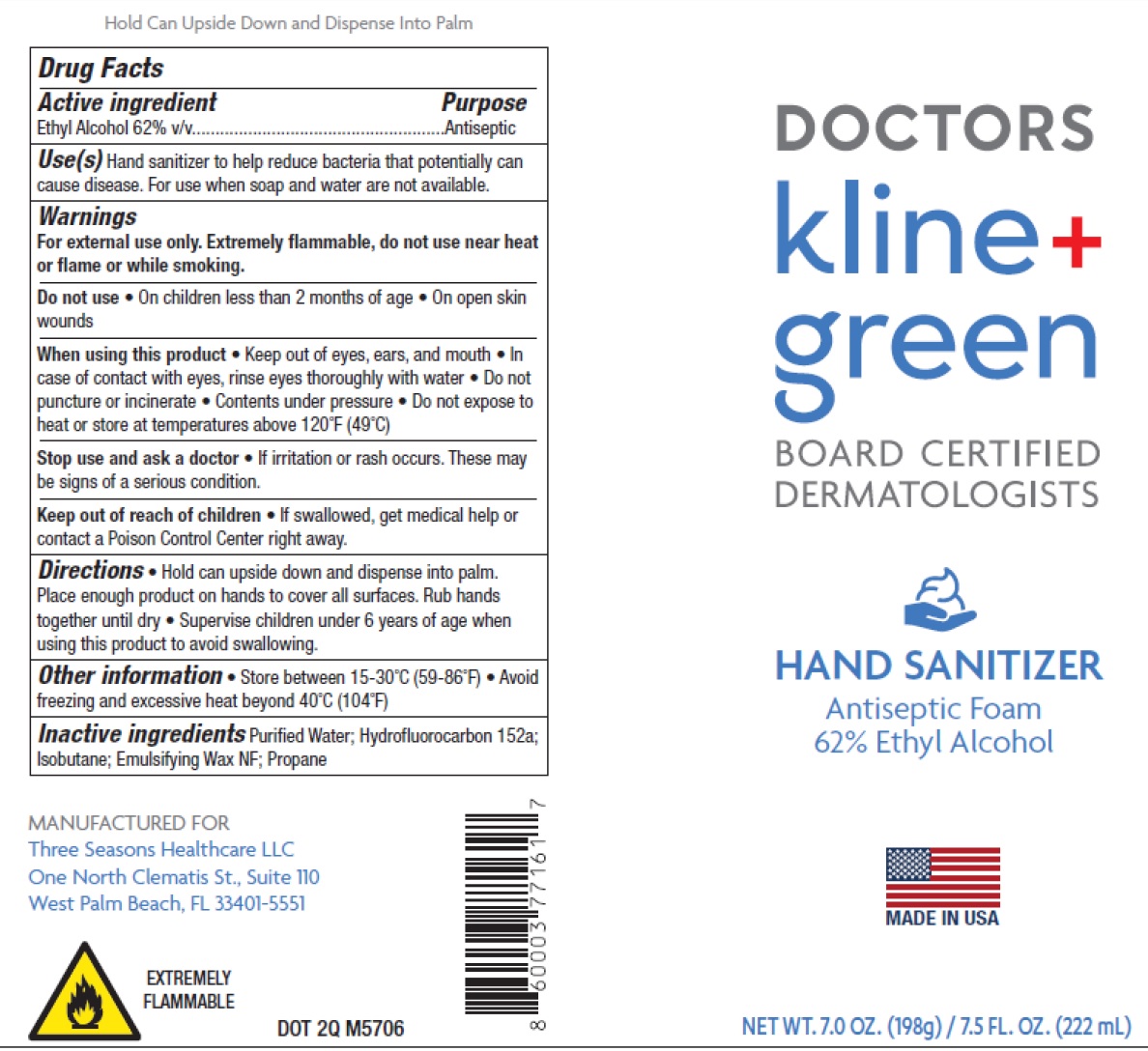 DRUG LABEL: Doctors Kline and Green Board Certified Dermatologist Hand Sanitizer Antiseptic
NDC: 23667-104 | Form: AEROSOL, FOAM
Manufacturer: Formulated Solutions, LLC
Category: otc | Type: HUMAN OTC DRUG LABEL
Date: 20231130

ACTIVE INGREDIENTS: ALCOHOL 62 mL/100 mL
INACTIVE INGREDIENTS: WATER; 1,1-DIFLUOROETHANE; ISOBUTANE; PROPANE

Doctors Kline & Green Board Certified Dermatologist Hand Sanitizer Antiseptic

Active ingredient

Ethyl Alcohol 62% v/v

Purpose

Antiseptic

Uses(s)

Hand sanitizer to help reduce bacteria that potentially can cause disease. For use when soap and water are not available.

Warnings

For external use only. Extermely flammable, do not use near heat or flame or while smoking.

Do not use

- On children less than 2 months of age
- On open skin wounds

When using this product

- keep out of eyes, ears, and mouth
- In case of contact with eyes, rinse eyes thoroughly with water.
- Do not puncture or incinerate
- Contents under pressure
- Do not expose to heat or store at temperature above 120°F (49°C)

Stop use and ask a doctor

- If irritation or rash occurs. These may be signs of a serious condition.

Keep out of reach of children.

If swallowed, get medical help or contact a Poison Control Center right away.

Directions

- Hold can upside down and dispense into palm. Place enough product on hands to cover all surfaces. Rub hands together until dry
- Supervise children under 6 years of age when using this product to avoid swallowing.

Other information

- Store between 15-30°C (59-86°F)
- Avoid freezing and excessive heat beyond 40°C (104°F)

Inactive ingredients

Purified Water, Hydrofluorocarbon 152a; Isobutane; Emulsifying Wax NF; Propane